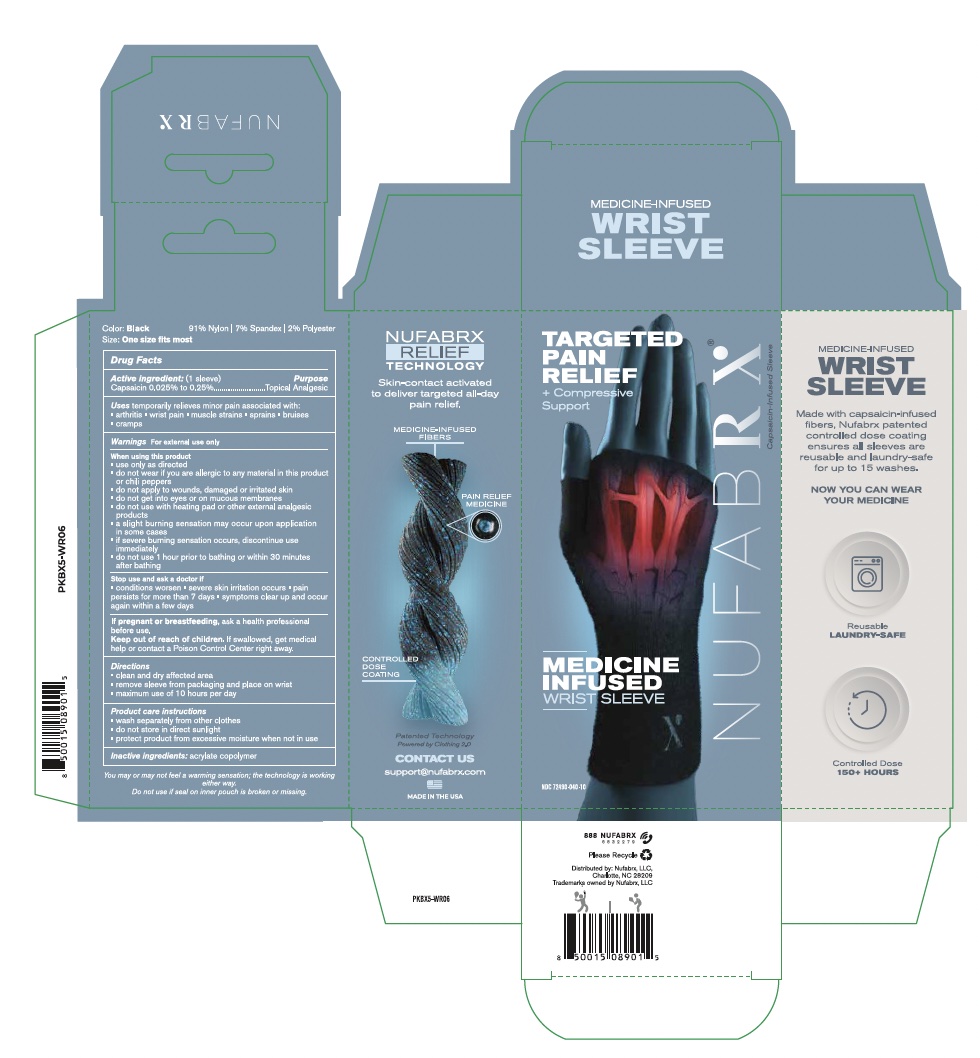 DRUG LABEL: Nufabrx Medicine Infused Wrist Sleeve
NDC: 72490-040 | Form: CLOTH
Manufacturer: Nufabrx LLC
Category: otc | Type: HUMAN OTC DRUG LABEL
Date: 20251015

ACTIVE INGREDIENTS: CAPSAICIN 0.25 g/100 g
INACTIVE INGREDIENTS: BUTYL ACRYLATE/METHYL METHACRYLATE/METHACRYLIC ACID COPOLYMER (18000 MW)

Nufabrx Medicine Infused Wrist Sleeve 72490-040

Active Ingredient

Capsaicin 0.025% to 0.25%

Purpose

Topical Analgesic

Uses

Temporarily relieves minor pain associated with:

- arthritis
- wrist pain
- muscle strains
- sprains
- bruises
- cramps

Directions

- Clean and dry affected area
- Remove sleeve from packaging and place on wrist
- wash hands after applying

Product Care Instructions

- Machine wash cold, separately, gentle cycle, mild detergent, tumble dry low
- do not bleach, do not iron, do not dry clean
- Do not store in direct sunlight, protect product from excessive moisture when not in use

Inactive Ingredients

Acrylate Copolymer

Changes to Directions

Replaced Maximum use of 10 hours per day with wash hands after applying

Warnings

For external use only

Keep out of reach of children

If swallowed, get medical help or contact a Poison Control Center right away.

If pregnant or breastfeeding

Ask a health professional before use.

When using this product

- Use only as directed
- Do not wear If you are allergic to any material in this product or chili peppers
- Do not apply on wounds, damaged or irritated skin
- Do not get into eyes or on mucous membranes
- Do not use with a heating pad or other external analgesic products
- A slight burning sensation may occur upon application in some cases
- If severe burning sensation occurs, discontinue use immediately

Stop use and ask a doctor if

- Condition worsens, symptoms
- Severe skin irriation occurs
- Pain persists more than 7 days
- Symptoms clear up and occur again within a few days